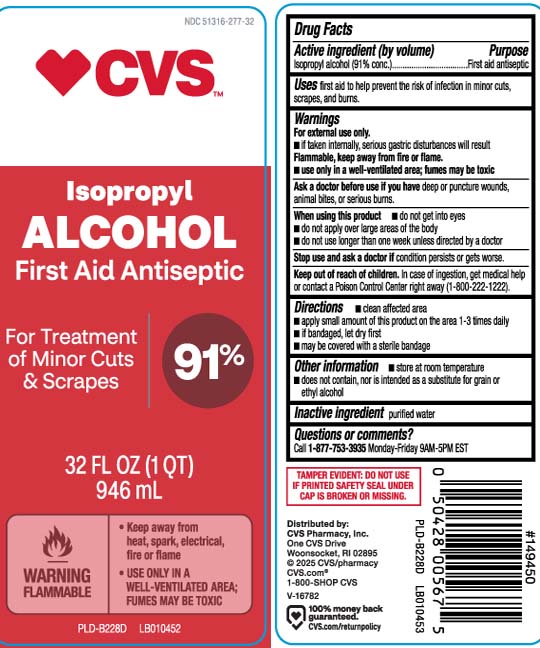 DRUG LABEL: Isopropyl Alcohol
NDC: 51316-277 | Form: LIQUID
Manufacturer: CVS PHARMACY, INC
Category: otc | Type: HUMAN OTC DRUG LABEL
Date: 20251217

ACTIVE INGREDIENTS: ISOPROPYL ALCOHOL 91 mL/100 mL
INACTIVE INGREDIENTS: WATER

Drug Facts

Active ingredient (by volume)

Isopropyl alcohol (91% conc.)

Purpose

first aid antiseptic

Uses

first aid to help prevent the risk of infection in minor cuts, scrapes and burns

Warnings

For external use only

- if taken internally, serious gastric disturbances will result

flammable, keep away from fire or flame

- use only in a well-ventilated area; fumes may be toxic

Ask a doctor before use if you have

deep or puncture wounds, animal bites or serious burns

When using this product

- do not get into eyes
- do not apply over large areas of the body
- do not use longer than one week unless directed by a doctor

Stop use and ask a doctor if

condition persists or gets worse

Keep out of reach of children.

In case of ingestion, get medical help or contact a Poison Control Center right away (1-800-222-1222).

Directions

- clean affected area
- apply small amount of this product on the area 1-3 times daily
- if bandaged, let dry first
- may be covered with a sterile bandage

Other information

- store at room temperature
- does not contain, nor is intended as a substitute for grain or ethyl alcohol

Inactive ingredient

purified water

Questions or Comments?

Call 1-877-753-3935 Monday-Friday 9AM-5PM EST

Principal Display Panel

Isopropyl Alcohol 91%

FIRST AID ANTISEPTIC

For treatment of minor cuts & scrapes

WARNING: FLAMMABLE | • Keep away from heat, spark, electrical, fire or flame

- USE ONLY IN A WELL-VENTILATED AREA; FUMES MAY BE TOXIC

FL OZ (mL)

TAMPER EVIDENT: DO NOT USE IF PRINTED SAFETY SEAL UNDER CAP IS BROKEN OR MISSING

Distributed by:

CVS Pharmacy, Inc.

One CVS Drive Woonsocket, RI 02895

Package Label

CVS 91% Isopropyl Alcohol